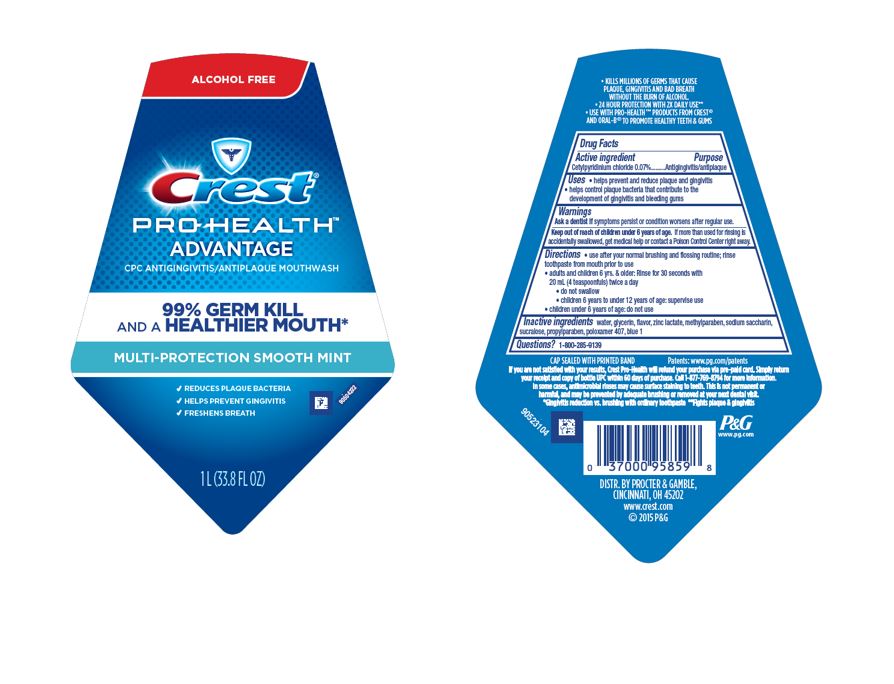 DRUG LABEL: Crest Pro-Health
NDC: 69423-893 | Form: RINSE
Manufacturer: The Procter & Gamble Manufacturing Company
Category: otc | Type: HUMAN OTC DRUG LABEL
Date: 20251211

ACTIVE INGREDIENTS: CETYLPYRIDINIUM CHLORIDE 0.07 g/1 mL
INACTIVE INGREDIENTS: PROPYLPARABEN; SUCRALOSE; GLYCERIN; ZINC LACTATE; METHYLPARABEN; SACCHARIN SODIUM; POLOXAMER 407; WATER; FD&C BLUE NO. 1

Crest PRO-HEALTH ADVANTAGE Rinse

Drug Facts

Active ingredient

Cetylpyridinium chloride 0.07%

Purpose

Antigingivitis/antiplaque

Uses

- helps prevent and reduce plaque and gingivitis
- helps control plaque bacteria that contribute to the development of gingivitis and bleeding gums

Warnings

ASK DOCTOR

Ask a dentist if symptoms persist or condition worsens after regular use.

Keep out of reach of children under 6 years of age. If more than used for rinsing is accidentally swallowed, get medical help or contact a Poison Control Center right away.

Directions

- use after your normal brushing and flossing routine; rinse toothpaste from mouth prior to use
- adults and children 6 yrs. & older: Rinse for 30 seconds with 20 mL (4 teaspoonfuls) twice a day
  - do not swallow
  - children 6 years to under 12 years of age: supervise use
- children under 6 years of age: do not use

Inactive ingredients

water, glycerin, flavor, zinc lactate, methylparaben, sodium saccharin, sucralose, propylparaben, poloxamer 407, blue 1

Questions?

1–800–285–9139

DISTR. BY PROCTER & GAMBLE,
CINCINNATI, OH 45202

Crest Pro Health Advantage Rinse 1L

ALCOHOL FREE

Crest ®
PRO-HEALTH™

ADVANTAGE
CPC ANTIGINGIVITIS/ANTIPLAQUE ORAL MOUTHWASH

99% GERM KILL

AND A HEALTHIER MOUTH*

MULTI-PROTECTION SMOOTH MINT

REDUCES PLAUE BACTERIA

HELPS PREVENT GINGIVITIS

FRESHENS BREATH

1 L (33.8 FL OZ)